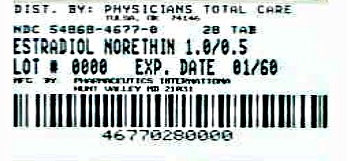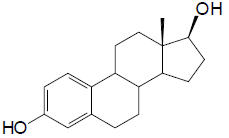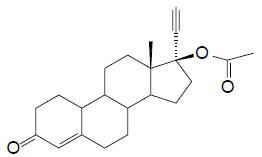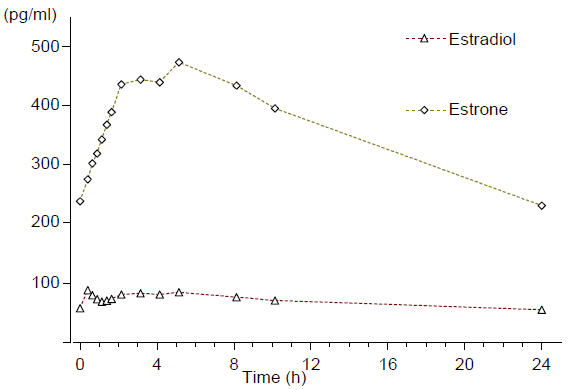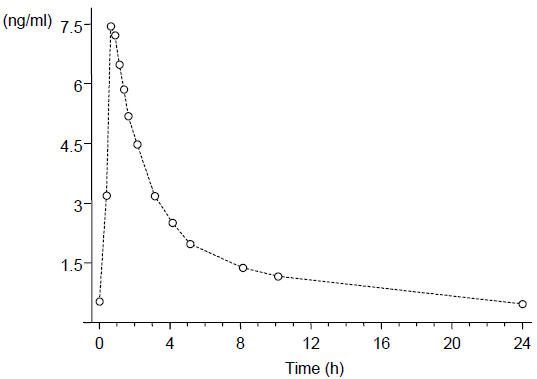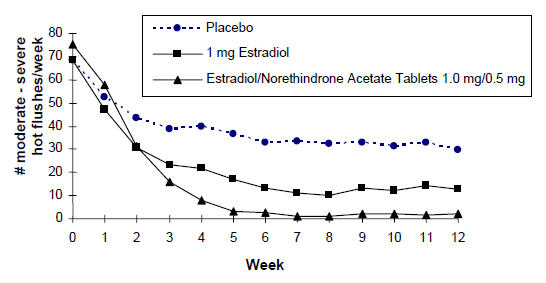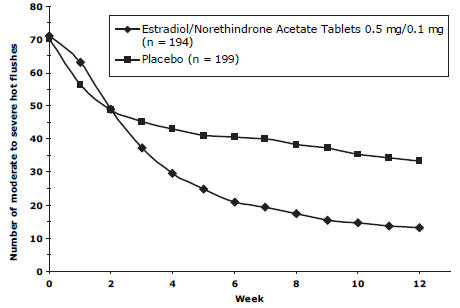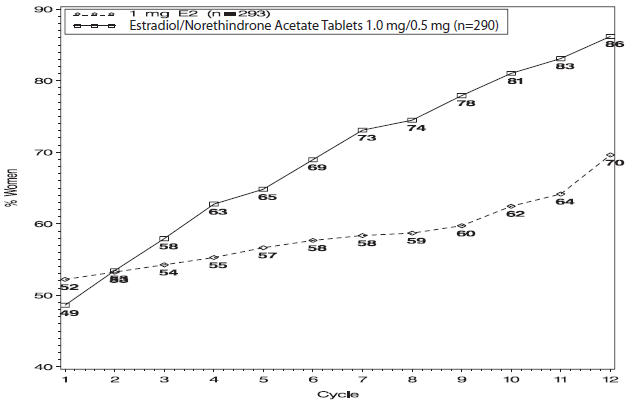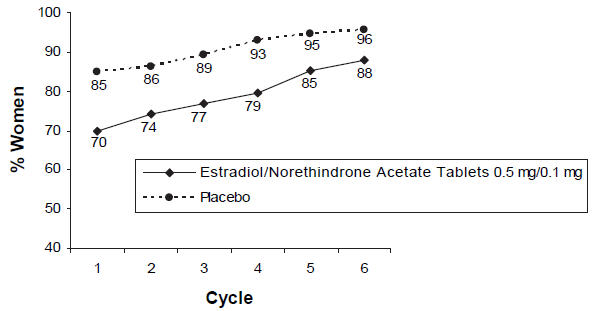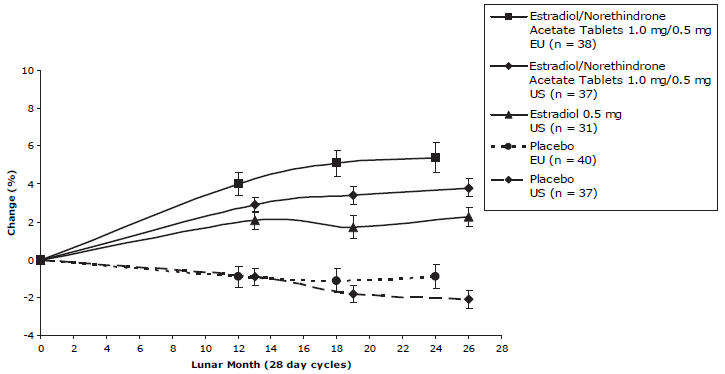 DRUG LABEL: Estradiol / Norethindrone Acetate
NDC: 54868-4677 | Form: TABLET, FILM COATED
Manufacturer: Physicians Total Care, Inc.
Category: prescription | Type: HUMAN PRESCRIPTION DRUG LABEL
Date: 20120829

ACTIVE INGREDIENTS: Estradiol 1 mg/1 1; Norethindrone Acetate 0.5 mg/1 1
INACTIVE INGREDIENTS: lactose monohydrate; starch, corn; copovidone; talc; magnesium stearate; hypromelloses; triacetin

Estradiol/Norethindrone Acetate Tablets

1.0 mg/0.5 mg
0.5 mg/0.1 mg

Rx only

CARDIOVASCULAR AND OTHER RISKS

Estrogens with or without progestins should not be used for the prevention of cardiovascular disease or dementia. (See CLINICAL STUDIES and WARNINGS, Cardiovascular disorders and Dementia.)

The estrogen plus progestin substudy of the Women's Health Initiative (WHI) reported increased risks of myocardial infarction, stroke, invasive breast cancer, pulmonary emboli, and deep vein thrombosis in postmenopausal women (50 to 79 years of age) during 5.6 years of treatment with oral conjugated estrogens (CE 0.625 mg) combined with medroxyprogesterone acetate (MPA 2.5 mg) per day, relative to placebo. (See CLINICAL STUDIES and WARNINGS, Cardiovascular disorders and Malignant neoplasms, Breast cancer.)

The estrogen-alone substudy of the WHI reported increased risks of stroke and deep vein thrombosis (DVT) in postmenopausal women (50 to 79 years of age) during 6.8 years and 7.1 years, respectively, of treatment with oral conjugated estrogens (CE 0.625 mg) per day, relative to placebo. (See CLINICAL STUDIES and WARNINGS, Cardiovascular disorders.)

The Women's Health Initiative Memory Study (WHIMS), a substudy of the WHI study, reported increased risk of developing probable dementia in postmenopausal women 65 years of age or older during 4 years of treatment with CE 0.625 mg combined with MPA 2.5 mg and during 5.2 years of treatment with CE 0.625 mg alone, relative to placebo. It is unknown whether this finding applies to younger postmenopausal women. (See CLINICAL STUDIES, WARNINGS, Dementia and PRECAUTIONS, Geriatric Use.)

Other doses of oral conjugated estrogens with medroxyprogesterone acetate, and other combinations and dosage forms of estrogens and progestins were not studied in the WHI clinical trials and, in the absence of comparable data, these risks should be assumed to be similar. Because of these trials, estrogens with or without progestins should be prescribed at the lowest effective doses and for the shortest duration consistent with treatment goals and risks for the individual woman.

DESCRIPTION

Estradiol/Norethindrone Acetate Tablets 1.0 mg/0.5 mg is a single tablet for oral administration containing 1 mg of estradiol and 0.5 mg of norethindrone acetate and the following excipients: lactose monohydrate, starch (corn), copovidone, talc, magnesium stearate, hypromellose and triacetin.

Estradiol/Norethindrone Acetate Tablets 0.5 mg/0.1 mg is a single tablet for oral administration containing 0.5 mg of estradiol and 0.1 mg of norethindrone acetate and the following excipients: lactose monohydrate, starch (corn), copovidone, talc, magnesium stearate, hypromellose and triacetin.

Estradiol (E2) is a white or almost white crystalline powder. Its chemical name is estra-1, 3, 5 (10)-triene-3, 17β-diol hemihydrate with the empirical formula of C18H24O2, ½ H2O and a molecular weight of 281.4. The structural formula of E2 is as follows:

Estradiol

Norethindrone acetate (NETA) is a white or yellowish-white crystalline powder. Its chemical name is 17β-acetoxy-19-nor-17α-pregn-4-en-20-yn-3-one with the empirical formula of C22H28O3 and molecular weight of 340.5. The structural formula of NETA is as follows:

Norethindrone Acetate

CLINICAL PHARMACOLOGY

Endogenous estrogens are largely responsible for the development and maintenance of the female reproductive system and secondary sexual characteristics. Although circulating estrogens exist in a dynamic equilibrium of metabolic interconversions, estradiol is the principal intracellular human estrogen and is substantially more potent than its metabolites, estrone and estriol, at the receptor level.

The primary source of estrogen in normally cycling adult women is the ovarian follicle, which secretes 70 to 500 mcg of estradiol daily, depending on the phase of the menstrual cycle. After menopause, most endogenous estrogen is produced by conversion of androstenedione, secreted by the adrenal cortex, to estrone by peripheral tissues. Thus, estrone and the sulfate conjugated form, estrone sulfate, are the most abundant circulating estrogens in postmenopausal women.

Estrogens act through binding to nuclear receptors in estrogen-responsive tissues. To date, two estrogen receptors have been identified. These vary in proportion from tissue to tissue.

Circulating estrogens modulate the pituitary secretion of the gonadotropins, luteinizing hormone (LH), and follicle-stimulating hormone (FSH) through a negative feedback mechanism. Estrogens act to reduce the elevated levels of these hormones seen in postmenopausal women.

Progestin compounds enhance cellular differentiation and generally oppose the actions of estrogens by decreasing estrogen receptor levels, increasing local metabolism of estrogens to less active metabolites, or inducing gene products that blunt cellular responses to estrogen. Progestins exert their effects in target cells by binding to specific progesterone receptors that interact with progesterone response elements in target genes. Progesterone receptors have been identified in the female reproductive tract, breast, pituitary, hypothalamus, and central nervous system. Progestins produce similar endometrial changes to those of the naturally occurring hormone progesterone.

PHARMACOKINETICS

A. Absorption

Estradiol is well absorbed through the gastrointestinal tract. Following oral administration of Estradiol/Norethindrone Acetate tablets, peak plasma estradiol concentrations are reached slowly within 5-8 hours. When given orally, estradiol is extensively metabolized (first-pass effect) to estrone sulfate, with smaller amounts of other conjugated and unconjugated estrogens. After oral administration, norethindrone acetate is rapidly absorbed and transformed to norethindrone. It undergoes first-pass metabolism in the liver and other enteric organs, and reaches a peak plasma concentration within 0.5 - 1.5 hours after the administration of Estradiol/Norethindrone Acetate tablets. The oral bioavailability of estradiol and norethindrone following administration of Estradiol/Norethindrone Acetate Tablets 1.0 mg/0.5 mg when compared to a combination oral solution is 53% and 100%, respectively. Administration of Estradiol/Norethindrone Acetate Tablets 1.0 mg/0.5 mg with food did not modify the bioavailability of estradiol, although increases in AUC0-72 of 19% and decreases in Cmax of 36% for norethindrone were seen. The pharmacokinetic parameters of estradiol (E2), estrone (E1), and norethindrone (NET) following oral administration of 1 Estradiol/Norethindrone Acetate Tablets 1.0 mg/0.5 mg or 2 Estradiol/Norethindrone Acetate 0.5 mg/0.1 mg tablet(s) to healthy postmenopausal women are summarized in Table 1.

TABLE 1 PHARMACOKINETIC PARAMETERS AFTER ADMINISTRATION OF 1 TABLET OF ESTRADIOL/NORETHINDRONE ACETATE 1.0 MG/0.5 MG OR 2 TABLETS OF ESTRADIOL/NORETHINDRONE ACETATE 0.5 MG/0.1 MG TO HEALTHY POSTMENOPAUSAL WOMEN
 | 1 × Estradiol/Norethindrone Acetate Tablets | 2 × Estradiol/Norethindrone Acetate Tablets
 | 1.0 mg/0.5 mg | 0.5 mg/0.1 mg
 | (n=24) | (n=24)
 | Mean [geometric mean;] (%CV) [geometric % coeffient of variation;] | Mean(%CV)
Estradiol [baseline unadjusted data;] (E 2)
AUC 0-t (pg/mL*h) | 766.5 (48) | 697.3 (53)
C max (pg/mL) | 26.8 (36) | 26.5 (37)
t max (h): median (range) | 6.0 (0.5-16.0) | 6.5 (0.5-16.0)
t1/2 (h) [baseline unadjusted data ;] | 14.0 (29) | 14.5 (27)
Estrone (E 1)
AUC 0-t(pg/mL*h) | 4469.1 (48) | 4506.4 (44)
C max (pg/mL) | 195.5 (37) | 199.5 (30)
t max (h): median (range) | 6.0 (1.0-9.0) | 6.0 (2.0-9.0)
t 1/2 (h) | 10.7 (44) [n=13;] | 11.8 (25)
Norethindrone (NET)
AUC 0-t (pg/mL*h) | 21043 (41) | 8407.2 (43)
C max (pg/mL) | 5249.5 (47) | 2375.4 (41)
t max (h): median (range) | 0.7 (0.7-1.25) | 0.8 (0.7-1.3)
t 1/2 (h) | 9.8 (32) | 11.4 (36)
AUC = area under the curve, 0 – last quantifiable sample
C max = maximum plasma concentration,
tmax = time at maximum plasma concentration,
t1/2 = half-life,

Following continuous dosing with once-daily administration of Estradiol/Norethindrone Acetate Tablets 1.0 mg/0.5 mg, serum levels of estradiol, estrone, and norethindrone reached steady-state within two weeks with an accumulation of 33-47% above levels following single dose administration. Unadjusted circulating levels of E2, E1, and NET during Estradiol/Norethindrone Acetate Tablets 1.0 mg/0.5 mg treatment at steady state (dosing at time 0) are provided in Figures 1a and 1b.

Figure 1a Levels of Estradiol and Estrone at Steady State During Continuous Dosing with Estradiol/Norethindrone Acetate Tablets 1.0 mg/0.5 mg (n=24)

Figure 1b Levels of Norethindrone at Steady State During Continuous Dosing with Estradiol/Norethindrone Acetate Tablets 1.0 mg/0.5 mg (n=24)

B. Distribution

The distribution of exogenous estrogens is similar to that of endogenous estrogens. Estrogens are widely distributed in the body and are generally found in higher concentrations in the sex hormone target organs. Estradiol circulates in the blood bound to sex-hormone-binding globulin (SHBG) (37%) and to albumin (61%), while only approximately 1-2% is unbound. Norethindrone also binds to a similar extent to SHBG (36%) and to albumin (61%).

C. Metabolism

Estradiol

Exogenous estrogens are metabolized in the same manner as endogenous estrogens. Circulating estrogens exist in a dynamic equilibrium of metabolic interconversions. These transformations take place mainly in the liver. Estradiol is converted reversibly to estrone, and both can be converted to estriol, which is the major urinary metabolite. Estrogens also undergo enterohepatic recirculation via sulfate and glucuronide conjugation in the liver, biliary secretion of conjugates into the intestine, and hydrolysis in the intestine followed by reabsorption. In postmenopausal women, a significant proportion of the circulating estrogens exist as sulfate conjugates, especially estrone sulfate, which serves as a circulating reservoir for the formation of more active estrogens.

Norethindrone Acetate

The most important metabolites of norethindrone are isomers of 5α-dihydro-norethindrone and tetrahydro-norethindrone, which are excreted mainly in the urine as sulfate or glucuronide conjugates.

D. Excretion

Estradiol, estrone, and estriol are excreted in the urine along with glucuronide and sulfate conjugates. The half-life of estradiol following single dose administration of Estradiol/Norethindrone Acetate Tablets 1.0 mg/0.5 mg is 12-14 hours. The terminal half-life of norethindrone is about 8-11 hours.

E. Special Populations

No pharmacokinetic studies were conducted in special populations, including patients with renal or hepatic impairment.

F. Drug Interactions

Coadministration of estradiol with norethindrone acetate did not elicit any apparent influence on the pharmacokinetics of norethindrone. Similarly, no relevant interaction of norethindrone on the pharmacokinetics of estradiol was found within the NETA dose range investigated in a single dose study.

In-vitro and in-vivo studies have shown that estrogens are metabolized partially by cytochrome P450 3A4 (CYP3A4). Therefore, inducers or inhibitors of CYP3A4 may affect estrogen drug metabolism. Inducers of CYP3A4 such as St. John's Wort preparations (Hypericum perforatum), phenobarbital, carbamazepine, and rifampin may reduce plasma concentrations of estrogens, possibly resulting in a decrease in therapeutic effects and/or changes in the uterine bleeding profile. Inhibitors of CYP3A4 such as erythromycin, clarithromycin, ketoconazole, itraconazole, ritonavir and grapefruit juice may increase plasma concentrations of estrogens and result in side effects.

CLINICAL STUDIES

Effects on Vasomotor Symptoms

In a 12-week randomized clinical trial involving 92 subjects, Estradiol/Norethindrone Acetate Tablets 1.0 mg/0.5 mg was compared to 1 mg of estradiol and to placebo. The mean number and intensity of hot flushes were significantly reduced from baseline to week 4 and 12 in both the Estradiol/Norethindrone Acetate Tablets 1.0 mg/0.5 mg and the 1 mg estradiol group compared to placebo (see Figure 2).

Figure 2 Mean Weekly Number of Moderate and Severe Hot Flushes in a 12-Week Study

In a study conducted in Europe a total of 577 postmenopausal women were randomly assigned to either Estradiol/Norethindrone Acetate Tablets 0.5 mg/0.1 mg, 0.5 mg E2/0.25 mg NETA, or placebo for 24 weeks of treatment. The mean number and severity of hot flushes were significantly reduced at week 4 and week 12 in the Estradiol/Norethindrone Acetate Tablets 0.5 mg/0.1 mg (see Figure 3) and 0.5 mg E2/0.25 mg NETA groups compared to placebo.

Figure 3 Mean Number of Moderate to Severe Hot Flushes for Weeks 0 Through 12

Effects on the Endometrium

Estradiol/Norethindrone Acetate Tablets 1.0 mg/0.5 mg reduced the incidence of estrogen-induced endometrial hyperplasia at 1 year in a randomized, controlled clinical trial. This trial enrolled 1,176 subjects who were randomized to one of 4 arms: 1 mg estradiol unopposed (n=296), 1 mg E2 + 0.1 mg NETA (n=294), 1 mg E2 + 0.25 mg NETA (n=291), and Estradiol/Norethindrone Acetate Tablets 1.0 mg/0.5 mg (n=295). At the end of the study, endometrial biopsy results were available for 988 subjects. The results of the 1 mg estradiol unopposed arm compared to Estradiol/Norethindrone Acetate Tablets 1.0 mg/0.5 mg are shown in Table 2.

TABLE 2 INCIDENCE OF ENDOMETRIAL HYPERPLASIA WITH UNOPPOSED ESTRADIOL AND ESTRADIOL/ NORETHINDRONE ACETATE TABLETS 1.0 MG/0.5 MG IN A 12-MONTH STUDY
 | 1 mg E 2 (n=296) | Estradiol/Norethindrone Acetate Tablets 1 mg E2/0.50mg NETA (n=295) | 1 mg E2/0.25 mg NETA (n=291) | 1 mg E2/0.1 mg NETA (n=294)
No. of subjects with histological evaluation at the end of the study | 247 | 241 | 251 | 249
No. (%) of subjects with endometrial hyperplasia at the end of the study | 36 (14.6%) | 1 (0.4%) | 1 (0.4%) | 2 (0.8%)

Effects on Uterine Bleeding or Spotting

During the initial months of therapy, irregular bleeding or spotting occurred with Estradiol/Norethindrone Acetate Tablets 1.0 mg/0.5 mg treatment. However, bleeding tended to decrease over time, and after 12 months of treatment with Estradiol/Norethindrone Acetate Tablets 1.0 mg/0.5 mg, about 86% of women were amenorrheic (see Figure 4).

Figure 4 Patients Treated with Estradiol/Norethindrone Acetate Tablets 1.0 mg/0.5 mg with Cumulative Amenorrhea over Time Percentage of Women with no Bleeding or Spotting at any Cycle Through Cycle 13 Intent to Treat Population, LOCF

Note: the percentage of patients who were amenorrheic in a given cycle and through cycle 13 is shown. If data were missing, the bleeding value from the last reported day was carried forward (LOCF).

In the clinical trial with Estradiol/Norethindrone Acetate Tablets 0.5 mg/0.1 mg, 88% of women were amenorrheic after 6 months of treatment (see Figure 5).

Figure 5 Patients Treated with Estradiol/Norethindrone Acetate Tablets 0.5 mg/0.1 mg with Cumulative Amenorrhea over Time Percentage of Women with no Bleeding or Spotting at any Cycle Through Cycle 6, Intent to Treat Population, LOCF

Effects on Bone Mineral Density

The results of two randomized, multicenter, calcium-supplemented (500-1000 mg/day), placebo-controlled, 2 year clinical trials have shown that Estradiol/Norethindrone Acetate Tablets 1.0 mg/0.5 mg and estradiol 0.5 mg are effective in preventing bone loss in postmenopausal women. While Estradiol/Norethindrone Acetate Tablets 0.5 mg/0.1 mg was not directly studied in these trials, the US trial showed that addition of NETA to estradiol enhances the effect on BMD, therefore the BMD changes expected from treatment with Estradiol/Norethindrone Acetate Tablets 0.5 mg/0.1 mg should be at least as great as observed with estradiol 0.5 mg. A total of 462 postmenopausal women with intact uteri and baseline BMD values for lumbar spine within 2 standard deviations of the mean in healthy young women were enrolled. In a US trial, 327 postmenopausal women (mean time from menopause 2.5 to 3.1 years) with a mean age of 53 years were randomized to 7 groups (0.25 mg, 0.5 mg, and 1 mg of estradiol alone, 1 mg estradiol with 0.25 mg norethindrone acetate, 1 mg estradiol with 0.5 mg norethindrone acetate, and 2 mg estradiol with 1 mg norethindrone acetate, and placebo.) In a European trial (EU trial), 135 postmenopausal women (mean time from menopause 8.4 to 9.3 years) with a mean age of 58 years were randomized to 1 mg estradiol with 0.25 mg norethindrone acetate, 1 mg estradiol with 0.5 mg norethindrone acetate, and placebo. Approximately 58% and 67% of the randomized subjects in the two clinical trials, respectively, completed the two clinical trials. BMD was measured using dual-energy x-ray absorptiometry (DEXA).

A summary of the results comparing Estradiol/Norethindrone Acetate Tablets 1.0 mg/0.5 mg and estradiol 0.5 mg to placebo from the two prevention trials is shown in Table 3.

TABLE 3 PERCENTAGE CHANGE (MEAN ± SD) IN BONE MINERAL DENSITY (BMD) FOR ESTRADIOL/ NORETHINDRONE ACETATE TABLETS 1.0 MG/0.5 MG AND 0.5 MG E2 [While Estradiol/Norethindrone Acetate Tablets 0.5 mg/0.1 mg was not directly studied in these trials, the US trial showed that addition of NETA to estradiol enhances the effect on BMD, therefore the BMD changes expected from treatment with Estradiol/Norethindrone Acetate Tablets 0.5 mg/0.1 mg should be at least as great as observed with estradiol 0.5 mg.] (Intent to Treat Analysis, Last Observation Carried Forward)
 | US Trial |  |  | EU Trial
 |  |  | Estradiol/Norethindrone |  | Estradiol/Norethindrone
 | Placebo (n=37) | 0.5 mg E 2 (n=31) | Acetate Tablets 1.0 mg/0.5 mg (n=37) | Placebo (n=40) | Acetate Tablets 1.0 mg/0.5 mg (n=38)
Lumbar spine | -2.1 ± 2.9 | 2.3 ± 2.8 [Significantly (p<0.001) different from placebo] | 3.8 ± 3.0 | -0.9 ± 4.0 | 5.4 ± 4.8
Femoral neck | -2.3 ± 3.4 | 0.3 ± 2.9 | 1.8 ± 4.1 | -1.0 ± 4.6 | 0.7 ± 6.1
Femoral trochanter | -2.0 ± 4.3 | 1.7 ± 4.1 | 3.7 ± 4.3 | 0.8 ± 6.9 | 6.3 ± 7.6
US= United States, EU = European

The overall difference in mean percentage change in BMD at the lumbar spine in the US trial (1000 mg/day calcium) between Estradiol/Norethindrone Acetate Tablets 1.0 mg/0.5 mg and placebo was 5.9% and between estradiol 0.5 mg and placebo was 4.4%. In the European trial (500 mg/day calcium), the overall difference in mean percentage change in BMD at the lumbar spine was 6.3%. Estradiol/Norethindrone Acetate Tablets 1.0 mg/0.5 mg and estradiol 0.5 mg also increased BMD at the femoral neck and femoral trochanter compared to placebo. The increase in lumbar spine BMD in the US and European clinical trials for Estradiol/Norethindrone Acetate Tablets 1.0 mg/0.5 mg and estradiol 0.5 mg is displayed in Figure 6.

Figure 6 Percentage Change in Bone Mineral Density (BMD) ± SEM of the Lumbar Spine (L1-L4) for Estradiol/Norethindrone Acetate Tablets 1.0 MG/0.5 MG and Estradiol 0.5 MG (Intent to Treat Analysis with Last Observation Carried Forward)

Effect on Bone Turnover

Estradiol/Norethindrone Acetate Tablets 1.0 mg/0.5 mg reduced serum and urine markers of bone turnover with a marked decrease in bone resorption markers (e.g., urinary pyridinoline crosslinks Type 1 collagen C- telopeptide, pyridinoline, deoxypyridinoline) and to a lesser extent in bone formation markers (e.g., serum osteocalcin, bone-specific alkaline phosphatase, C-terminal propetide of type 1 collagen). The suppression of bone turnover markers was evident by 3 months and persisted throughout the 24-month treatment period.

Treatment with 0.5 mg estradiol decreased biochemical markers of bone resorption (urinary pyridinoline, urinary deoxypyridinoline) and bone formation (bone-specific alkaline phosphatase) compared to placebo. These decreases occurred by 6 months of treatment after which the levels were maintained throughout the 24 months.

Women's Health Initiative Studies

The WHI enrolled a total of 27,000 predominantly healthy postmenopausal women in two substudies to assess the risks and benefits of either the use of oral conjugated estrogens (CE 0.625 mg per day) alone or the use of oral conjugated estrogens (CE 0.625 mg) plus medroxyprogesterone acetate (MPA 2.5 mg per day) compared to placebo in the prevention of certain chronic diseases. The primary endpoint was the incidence of coronary heart disease (CHD) (nonfatal myocardial infarction (MI), silent MI and CHD death), with invasive breast cancer as the primary adverse outcome studied. A "global index" included the earliest occurrence of CHD, invasive breast cancer, stroke, pulmonary embolism (PE), endometrial cancer, colorectal cancer, hip fracture, or death due to other cause. The study did not evaluate the effects of CE or CE/MPA on menopausal symptoms.

The estrogen-plus-progestin substudy was stopped early. According to the predefined stopping rule, after an average follow-up of 5.2 years of treatment, the increased risk of breast cancer and cardiovascular events exceeded the specified benefits included in the "global index." The absolute excess risk of events included in the "global index" was 19 per 10,000 women-years (RR 1.15, 95% nCI 1.03-1.28).

For those outcomes included in the WHI "global index," that reached statistical significance after 5.6 years of follow-up, the absolute excess risks per 10,000 women-years in the group treated with CE/MPA were six more CHD events, seven more strokes, ten more PEs, and eight more invasive breast cancers, while the absolute risk reductions per 10,000 women-years were seven fewer colorectal cancers and five fewer hip fractures. (See BOXED WARNINGS, WARNINGS, and PRECAUTIONS.)

Results of the estrogen-plus-progestin substudy, which included 16,608 women (average age of 63 years, range 50 to 79; 83.9 % White, 6.8 % Black, 5.4 % Hispanic, 3.9% Other) are presented in Table 4 below:

TABLE 4 RELATIVE AND ABSOLUTE RISK SEEN IN THE ESTROGEN-PLUS-PROGESTIN SUBSTUDY OF WHI AT AN AVERAGE OF 5.6 YEARS
Event | Relative Risk CE/MPA vs. Placebo (95% nCI) | CE/MPA n = 8,506 | Placebo n = 8,102
 |  | Absolute Risk per 10,000 Women-years
CHD events | 1.24 (1.00-1.54) | 39 | 33
Non-fatal MI | 1.28 (1.00-1.63) | 31 | 25
CHD death | 1.10 (0.70-1.75) | 8 | 8
All strokes | 1.31 (1.02–1.68) | 31 | 24
Ischemic stroke | 1.44 (1.09–1.90) | 26 | 18
Deep vein thrombosis | 1.95 (1.43–2.67) | 26 | 13
Pulmonary embolism | 2.13 (1.45–3.11) | 18 | 8
Invasive breast cancer | 1.24 (1.01–1.54) | 41 | 33
Invasive colorectal cancer | 0.56 (0.38–0.81) | 9 | 16
Endometrial cancer | 0.81 (0.48–1.36) | 6 | 7
Cervical cancer | 1.44 (0.47–4.42) | 2 | 1
Hip fracture | 0.67 (0.47–0.96) | 11 | 16
Vertebral fractures | 0.65 (0.46–0.92) | 11 | 17
Lower arm/wrist fractures | 0.71 (0.59–0.85) | 44 | 62
Total fractures | 0.76 (0.69–0.83) | 152 | 199

The estrogen-alone substudy was also stopped early because an increased risk of stroke was observed, and it was deemed that no further information would be obtained regarding the risks and benefits of estrogen alone in predetermined primary endpoints. Results of the estrogen-alone substudy, which included 10,739 women (average age of 63 years, range 50 to 79; 75.3 % White, 15.1 % Black, 6.1 % Hispanic, 3.6% Other), after an average follow-up of 6.8 years are presented in Table 5 below.

TABLE 5 RELATIVE AND ABSOLUTE RISK SEEN IN THE ESTROGEN-ALONE SUBSTUDY OF WHI [Nominal confidence intervals unadjusted for multiple looks and multiple comparisons.]
Event | Relative Risk CE vs. Placebo | CE n = 5,310 | Placebo n = 5,429
 | (95% nCI) | Absolute Risk per 10,000 Women-years
CHD events [Results are based on centrally adjudicated data for an average follow-up of 7.1 years.] | 0.95 (0.79–1.16) | 53 | 56
Non-fatal MI | 0.91 (0.73–1.14) | 40 | 43
CHD death | 1.01(0.71–1.43) | 16 | 16
Stroke [Results are based on an average follow-up of 6.8 years.] | 1.39 (1.10-1.77) | 44 | 32
Deep vein thrombosis , [Not included in Global Index.] | 1.47 (1.06–2.06) | 23 | 15
Pulmonary embolism | 1.37 (0.90–2.07) | 14 | 10
Invasive breast cancer | 0.80 (0.62–1.04) | 28 | 34
Colorectal cancer | 1.08 (0.75–1.55) | 17 | 16
Hip fracture | 0.61 (0.41–0.91) | 11 | 17
Vertebral fractures , | 0.62 (0.42-0.93) | 11 | 17
Total fractures , | 0.70 (0.63-0.79) | 139 | 195
Death due to other causes , | 1.08 (0.88–1.32) | 53 | 50
Overall mortality , | 1.04 (0.88–1.22) | 81 | 78
Global Index , | 1.01 (0.91–1.12) | 192 | 190

For those outcomes included in the WHI "global index" that reached statistical significance, the absolute excess risk per 10,000 women-years in the group treated with estrogen-alone was 12 more strokes, while the absolute risk reduction per 10,000 women-years was six fewer hip fractures. The absolute excess risk of events included in the "global index" was a nonsignificant two events per 10,000 women-years. There was no difference between the groups in terms of all-cause mortality. (See BOXED WARNINGS, WARNINGS, and PRECAUTIONS.)

Final adjudicated results for CHD events from the estrogen-alone substudy, after an average follow-up of 7.1 years, reported no overall difference for primary CHD events (nonfatal MI, silent MI and CHD death) in women receiving CE alone compared with placebo (see Table 5).

Women's Health Initiative Memory Study

The estrogen plus progestin Women's Health Initiative Memory Study (WHIMS) substudy of WHI enrolled 4,532 predominantly healthy postmenopausal women 65 years of age and older (47 %, age 65 to 69 years, 35 %, age 70 to 74 years, 18 %, 75 years of age and older) to evaluate the effects of CE 0.625 mg plus MPA 2.5 mg daily on the incidence of probable dementia (primary outcome) compared with placebo.

After an average follow-up of four years, 40 women in the estrogen-plus-progestin group (45 per 10,000 women-years) and 21 in the placebo group (22 per 10,000 women-years) were diagnosed with probable dementia. The relative risk of probable dementia in the hormone therapy group was 2.05 (95 % CI, 1.21-3.48) compared to placebo. It is unknown whether these findings apply to younger postmenopausal women. (See BOXED WARNINGS, WARNINGS, Dementia, and PRECAUTIONS, Geriatric Use.)

The estrogen-alone WHIMS, a substudy of the WHI study, enrolled 2,947 predominantly healthy postmenopausal women 65 years of age and older (45 %, age 65 to 69 years, 36 %, age 70 to 74 years, 19 %, 75 years of age and older) to evaluate the effects of conjugated estrogens (CE 0.625 mg) on the incidence of probable dementia (primary outcome) compared with placebo.

After an average follow-up of 5.2 years, 28 women in the estrogen-alone group (37 per 10,000 women-years) and 19 in the placebo group (25 per 10,000 women-years) were diagnosed with probable dementia. The relative risk of probable dementia in the estrogen-alone group was 1.49 (95% CI 0.83-2.66) compared to placebo.

When data from the two populations were pooled as planned in the WHIMS protocol, the reported overall relative risk for probable dementia was 1.76 (95% CI 1.19-2.60). Differences between groups became apparent in the first year of treatment. It is unknown whether these findings apply to younger postmenopausal women. (See BOXED WARNINGS, WARNINGS, Dementia, and PRECAUTIONS, Geriatric Use.)

INDICATIONS AND USAGE

Estradiol/Norethindrone Acetate Tablets 1.0 mg/0.5 mg and 0.5 mg/0.1 mg are indicated in women who have a uterus for the:

1. Treatment of moderate to severe vasomotor symptoms associated with menopause.
2. Prevention of postmenopausal osteoporosis. When prescribing solely for the prevention of postmenopausal osteoporosis, therapy should only be considered for women at significant risk of osteoporosis and non-estrogen medications should be carefully considered.

The mainstays for decreasing the risk of postmenopausal osteoporosis are weight bearing exercise, adequate calcium and vitamin D intake, and when indicated, pharmacologic therapy. Postmenopausal women require an average of 1500 mg/day of elemental calcium. Therefore, when not contraindicated, calcium supplementation may be helpful for women with suboptimal dietary intake. Vitamin D supplementation of 400-800 IU/day may also be required to ensure adequate daily intake in postmenopausal women.

Estradiol/Norethindrone Acetate Tablets 1.0 mg/0.5 mg is also indicated in women who have a uterus for the:

3. Treatment of moderate to severe symptoms of vulvar and vaginal atrophy associated with menopause. When used solely for the treatment of symptoms of vulvar and vaginal atrophy, topical vaginal products should be considered.

CONTRAINDICATIONS

Estradiol/Norethindrone Acetate Tablets should not be used in women with any of the following conditions:

1. Undiagnosed abnormal genital bleeding.
2. Known, suspected, or history of cancer of the breast.
3. Known or suspected estrogen-dependent neoplasia.
4. Active deep vein thrombosis, pulmonary embolism, or history of these conditions.
5. Active or recent (e.g., within the past year) arterial thromboembolic disease (e.g., stroke, myocardial infarction).
6. Liver dysfunction or disease.
7. Known hypersensitivity to the ingredients of Estradiol/Norethindrone Acetate Tablets 1.0 mg/0.5 mg or Estradiol/Norethindrone Acetate Tablets 0.5 mg/0.1 mg.
8. Known or suspected pregnancy. There is no indication for Estradiol/Norethindrone Acetate Tablets in pregnancy. There appears to be little or no increased risk of birth defects in children born to women who have used estrogens and progestins from oral contraceptives inadvertently during early pregnancy. (See PRECAUTIONS.)

WARNINGS

See BOXED WARNINGS.

1. Cardiovascular disorders

Estrogen-plus-progestin therapy has been associated with an increased risk of myocardial infarction as well as stroke, venous thrombosis and pulmonary embolism.

Estrogen-alone therapy has been associated with an increased risk of stroke and deep vein thrombosis (DVT). Should any of these events occur or be suspected, estrogens should be discontinued immediately.

Risk factors for arterial vascular disease (e.g., hypertension, diabetes mellitus, tobacco use, hypercholesterolemia, and obesity) and/or venous thromboembolism (e.g., personal history or family history of VTE, obesity, and systemic lupus erythematosus) should be managed appropriately.

a. Stroke

In the estrogen plus progestin substudy of the Women's Health Initiative (WHI), a statistically significant increased risk of stroke was reported in women receiving CE/MPA 0.625 mg/2.5 mg daily compared to women receiving placebo (31 vs. 24 per 10,000 women-years). The increase in risk was demonstrated after the first year and persisted. (See CLINICAL STUDIES.)

In the estrogen-alone substudy of the WHI, a statistically significant increased risk of stroke was reported in women receiving CE 0.625 mg daily compared to women receiving placebo (44 vs. 32 per 10,000 women-years). The increase in risk was demonstrated in year one and persisted.

b. Coronary heart disease

In the estrogen-plus progestin sub-study of WHI, no statistically significant increase in CHD events (defined as non-fatal, MI, silent MI, or death, due to CHD) was reported in women receiving CE/MPA compared to women receiving placebo (39 vs. 33 per 10,000 women years). An increase in relative risk was demonstrated in year one, and a trend toward decreasing relative risk was reported in years 2 through 5. (See CLINICAL STUDIES.)

In the estrogen-alone substudy of WHI, no overall effect on coronary disease (CHD) events was reported in women receiving estrogen alone compared to placebo. (See CLINICAL STUDIES.)

In postmenopausal women with documented heart disease (n=2,763, average age 66.7 years), a controlled clinical trial of secondary prevention of cardiovascular disease (Heart and Estrogen/Progestin Replacement Study (HERS)) treatment with CE/MPA (0.625mg/2.5mg per day) demonstrated no cardiovascular benefit. During an average follow-up of 4.1 years, treatment with CE/MPA did not reduce the overall rate of CHD events in postmenopausal women with established coronary heart disease. There were more CHD events in the CE/MPA-treated group than in the placebo group in year 1, but not during the subsequent years. Participation in an open-label extension of the original HERS trial (HERS II) was agreed to by 2,321 women. Average follow-up in HERS II was an additional 2.7 years, for a total of 6.8 years overall. Rates of CHD events were comparable among women in the CE/MPA group and the placebo group in HERS, HERS II, and overall.

Large doses of estrogen (5 mg conjugated estrogens per day), comparable to those used to treat cancer of the prostate and breast, have been shown in a large prospective clinical trial in men to increase the risk of nonfatal myocardial infarction, pulmonary embolism, and thrombophlebitis.

c. Venous thromboembolism

In the estrogen-plus-progestin substudy of the Women's Health Initiative (WHI), a statistically significant 2-fold greater rate of VTE (DVT and pulmonary embolism [PE]), was reported in women receiving CE/MPA compared to women receiving placebo (35 vs. 17 per 10,000 women-years). Statistically significant increases in risk for both DVT (26 vs. 13 per 10,000 women-years) and PE (18 vs. 8 per 10,000 women-years) were also demonstrated. The increase in VTE risk was demonstrated during the first year and persisted. (See CLINICAL STUDIES.) In the estrogen-alone substudy of WHI, the risk of VTE was reported to be increased for women taking conjugated estrogens (30 vs. 22 per 10,000 women-years), although only the increased risk of DVT reached statistical significance (23 vs. 15 per 10,000 women-years). The increase in VTE risk was demonstrated during the first two years.

If feasible, estrogens should be discontinued at least 4 to 6 weeks before surgery of the type associated with an increased risk of thromboembolism, or during periods of prolonged immobilization.

2. Malignant neoplasms

a. Breast cancer

In some studies, the use of estrogens and progestins by postmenopausal women has been reported to increase the risk of breast cancer. The most important randomized clinical trial providing information about this issue is the CE/MPA substudy of the WHI study (see CLINICAL STUDIES). The results from observational studies are generally consistent with those of the WHI clinical trial.

Observational studies have also reported an increased risk of breast cancer for estrogen-plus-progestin combination therapy, and a smaller increased risk for estrogen-alone therapy, after several years of use. For both findings, the excess risk increased with duration of use, and appeared to return to baseline over about five years after stopping treatment (only the observational studies have substantial data on risk after stopping). In these studies, the risk of breast cancer was greater, and became apparent earlier, with estrogen-plus-progestin combination therapy as compared to estrogen-alone therapy. However, these studies have not found significant variation in the risk of breast cancer among different estrogens or among different estrogen-plus-progestin combinations, doses, or routes of administration.

In the estrogen-plus-progestin substudy, after a mean follow-up of 5.6 years, the WHI substudy reported an increased risk of breast cancer. In this substudy, prior use of estrogen alone or estrogen-plus-progestin combination hormone therapy was reported by 26% of the women. The relative risk of invasive breast cancer was 1.24 (95% nCI 1.01-1.54), and the absolute risk was 41 vs 33 cases per 10,000 women-years, for estrogen plus progestin compared with placebo, respectively. Among women who reported prior use of hormone therapy, the relative risk of invasive breast cancer was 1.86, and the absolute risk was 46 vs. 25 cases per 10,000 women-years, for estrogen plus progestin compared with placebo. Among women who reported no prior use of hormone therapy, the relative risk of invasive breast cancer was 1.09, and the absolute risk was 40 vs. 36 cases per 10,000 women-years of estrogen plus progestin compared with placebo. In the WHI trial, invasive breast cancers were larger and diagnosed at a more advanced stage in the estrogen-plus-progestin group compared with the placebo group. Metastatic disease was rare, with no apparent difference between the two groups. Other prognostic factors, such as histologic subtype, grade and hormone receptor status did not differ between the groups.

In the estrogen-alone substudy of WHI, after an average of 7.1 years of follow-up, CE (0.625 mg daily) was not associated with an increased risk of invasive breast cancer (RR 0.80, 95% nCI 0.62-1.04).

In a one-year trial among 1,176 women who received either unopposed 1 mg estradiol or a combination of 1 mg estradiol plus one of three different doses of NETA (0.1, 0.25, and 0.5 mg), seven new cases of breast cancer were diagnosed, two of which occurred among the group of 295 women treated with Estradiol/Norethindrone Acetate Tablets 1.0 mg/0.5 mg and two of which occurred among the group of 294 women treated with 1 mg estradiol/0.1 mg NETA.

The use of estrogen alone and estrogen plus progestin has been reported to result in an increase in abnormal mammograms requiring further evaluation. All women should receive yearly breast examinations by a health care provider and perform monthly breast self-examinations. In addition, mammography examinations should be scheduled based on patient age, risk factors, and prior mammogram results.

b. Endometrial cancer

The use of unopposed estrogens in women with intact uteri has been associated with an increased risk of endometrial cancer. The reported endometrial cancer risk among unopposed estrogen users is about 2- to 12- fold greater than in nonusers, and appears dependent on duration of treatment and on estrogen dose. Most studies show no significant increased risk associated with use of estrogens for less than one year. The greatest risk appears associated with prolonged use, with an increased risk of 15- to 24-fold for five to ten years or more. This risk has been shown to persist for at least 8 to 15 years after estrogen therapy is discontinued.

Clinical surveillance of all women taking estrogen/progestin combinations is important. Adequate diagnostic measures, including endometrial sampling when indicated, should be undertaken to rule out malignancy in all cases of undiagnosed persistent or recurring abnormal vaginal bleeding. There is no evidence that the use of natural estrogens results in a different endometrial risk profile than synthetic estrogens of equivalent estrogen dose. Adding a progestin to estrogen therapy has been shown to reduce the risk of endometrial hyperplasia, which may be a precursor to endometrial cancer.

Endometrial hyperplasia (a possible precursor of endometrial cancer) has been reported to occur in approximately 1% or less with Estradiol/Norethindrone Acetate Tablets in one large clinical trial.

3. Dementia

In the estrogen-plus-progestin Women's Health Initiative Memory Study (WHIMS), a substudy of WHI, a population of 4,532 postmenopausal women aged 65 to 79 years was randomized to CE/MPA (0.625 mg/2.5 mg daily) or placebo. In the estrogen-alone WHIMS substudy, a population of 2,947 hysterectomized women, aged 65 to 79 years, was randomized to CE (0.625 mg daily) or placebo.

In the estrogen-plus-progestin substudy, after an average follow-up of four years, 40 women in the estrogen-plus-progestin group and 21 women in the placebo group were diagnosed with probable dementia. The relative risk of probable dementia for estrogen plus progestin vs. placebo was 2.05 (95% CI 1.21-3.48). The absolute risk of probable dementia for CE/MPA vs. placebo was 45 vs. 22 cases per 10,000 women-years. In the estrogen-alone substudy, after an average follow-up of 5.2 years, 28 women in the estrogen-alone group and 19 women in the placebo group were diagnosed with probable dementia. The relative risk of probable dementia for CE alone vs. placebo was 1.49 (95% CI 0.83-2.66). The absolute risk of probable dementia for CE alone vs. placebo was 37 vs. 25 cases per 10,000 women-years.

When data from the two populations were pooled as planned in the WHIMS protocol, the reported overall relative risk of probable dementia was 1.76 (95% CI 1.19-2.60). Since both substudies were conducted in women ages 65 to 79, it is unknown whether these findings apply to younger postmenopausal women. (See BOXED WARNINGS and PRECAUTIONS, Geriatric Use.)

4. Gallbladder disease

A two- to four- fold increase in the risk of gallbladder disease requiring surgery in postmenopausal women receiving estrogens has been reported.

5. Hypercalcemia

Estrogen administration may lead to severe hypercalcemia in patients with breast cancer and bone metastases. If hypercalcemia occurs, use of the drug should be stopped and appropriate measures taken to reduce the serum calcium level.

6. Visual abnormalities

Retinal vascular thrombosis has been reported in patients receiving estrogens. Discontinue medication pending examination if there is a sudden partial or complete loss of vision, or a sudden onset of proptosis, diplopia, or migraine. If examination reveals papilledema or retinal vascular lesions, estrogens should be permanently discontinued.

PRECAUTIONS

A. General

1. Addition of a progestin when a woman has not had a hysterectomy.

Studies of the addition of a progestin for 10 or more days of a cycle of estrogen administration, or daily with estrogen in a continuous regimen, have reported a lowered incidence of endometrial hyperplasia than would be induced by estrogen treatment alone. Endometrial hyperplasia may be a precursor to endometrial cancer.

There are, however, possible risks that may be associated with the use of progestins with estrogens compared to estrogen-alone treatment. These include a possible increased risk of breast cancer.

2. Elevated blood pressure

In a small number of case reports, substantial increases in blood pressure have been attributed to idiosyncratic reactions to estrogens. In a large, randomized, placebo-controlled clinical trial, a generalized effect of estrogens on blood pressure was not seen. Blood pressure should be monitored at regular intervals with estrogen use.

3. Hypertriglyceridemia

In patients with pre-existing hypertriglyceridemia, estrogen therapy may be associated with elevations of plasma triglycerides leading to pancreatitis and other complications.

4. Impaired liver function and past history of cholestatic jaundice

Estrogens may be poorly metabolized in patients with impaired liver function. For patients with a history of cholestatic jaundice associated with past estrogen use or with pregnancy, caution should be exercised, and in the case of recurrence, medication should be discontinued.

5. Hypothyroidism

Estrogen administration leads to increased thyroid-binding globulin (TBG) levels. Patients with normal thyroid function can compensate for the increased TBG by making more thyroid hormone, thus maintaining free T4 and T3 serum concentrations in the normal range. Patients dependent on thyroid hormone replacement therapy who are also receiving estrogen may require increased doses of their thyroid replacement therapy. These patients should have their thyroid function monitored to maintain their free thyroid hormone levels in an acceptable range.

6. Fluid retention

Estrogens may cause some degree of fluid retention. Because of this, patients who have conditions that might be influenced by this factor, such as a cardiac or renal dysfunction, warrant careful observation when estrogens are prescribed.

7. Hypocalcemia

Estrogens should be used with caution in individuals with severe hypocalcemia.

8. Ovarian cancer

The estrogen-plus-progestin substudy of WHI reported that after an average follow-up of 5.6 years, the relative risk for ovarian cancer for estrogen plus progestin vs. placebo was 1.58 (95% CI 0.77 – 3.24), but was not statistically significant. The absolute risk for estrogen plus progestin vs. placebo was 4.2 vs. 2.7 cases per 10,000 women-years. In some epidemiologic studies, the use of estrogen-only products, in particular for 10 or more years, has been associated with an increased risk of ovarian cancer. Other epidemiologic studies have not found these associations.

9. Exacerbation of endometriosis

Endometriosis may be exacerbated with administration of estrogens.

Malignant transformation of residual endometrial implants has been reported in women treated post-hysterectomy with estrogen-alone therapy. For patients known to have residual endometriosis post-hysterectomy, the addition of progestin should be considered.

10. Exacerbation of other conditions

Estrogens may cause an exacerbation of asthma, diabetes mellitus, epilepsy, migraine or porphyria, systemic lupus erythematosus, and hepatic hemangiomas and should be used with caution in women with these conditions.

B. Patient Information

Physicians are advised to discuss the contents of the Patient Information leaflet with patients for whom they prescribe Estradiol/Norethindrone Acetate Tablets 1.0 mg/0.5 mg or Estradiol/Norethindrone Acetate Tablets 0.5 mg/0.1 mg.

C. Laboratory Tests

Estrogen administration should be initiated at the lowest dose approved for the indication and then guided by clinical response, rather than by serum hormone levels (e.g., estradiol, FSH).

D. Drug/laboratory Test Interactions

1. Accelerated prothrombin time, partial thromboplastin time, and platelet aggregation time; increased platelet count; increased factors II, VII antigen, VIII coagulant activity, IX, X, XII, VII-X complex, and beta-thromboglobulin; decreased levels of anti-factor Xa and antithrombin III, decreased antithrombin III activity, increased levels of fibrinogen and fibrinogen activity; increased Plasminogen antigen and activity.
2. Increased thyroid-binding globulin (TBG) levels leading to increased circulating total thyroid hormone levels as measured by protein-bound iodine (PBI), T4 levels (by column or by radioimmunoassay), or T3 levels by radioimmunoassay. T3 resin uptake is decreased, reflecting the elevated TBG. Free T4 and free T3 concent- rations are unaltered. Patients on thyroid replacement therapy may require higher doses of thyroid hormone.
3. Other binding proteins may be elevated in serum (i.e., corticosteroid binding globulin (CBG), SHBG) leading to increased total circulating corticosteroids and sex steroids, respectively. Free hormone concentrations may be decreased. Other plasma proteins may be increased (angiotensinogen/rennin substrate, alpha-1 antitrypsin, ceruloplasmin).
4. Increased plasma HDL and HDL2 cholesterol subfraction concentration, reduced LDL cholesterol concentration, increased triglyceride levels.
5. Impaired glucose tolerance.
6. Reduced response to metyrapone test.

E. Carcinogenesis, Mutagenesis, Impairment of Fertility

Long-term continuous administration of estrogen, with or without progestin, in women with or without a uterus, has shown an increased risk of endometrial cancer, breast cancer, and ovarian cancer. (See BOXED WARNINGS, WARNINGS, and PRECAUTIONS.)

Long-term continuous administration of natural and synthetic estrogens in certain animal species increases the frequency of carcinomas of the breast, uterus, cervix, vagina, testis, and liver.

F. Pregnancy

Estradiol/Norethindrone Acetate should not be used during pregnancy. (See CONTRAINDICATIONS.)

G. Nursing Mothers

Estrogen administration to nursing mothers has been shown to decrease the quantity and quality of breast milk. Detectable amounts of estrogens have been identified in the milk of mothers receiving this drug. Caution should be exercised when Estradiol/Norethindrone Acetate is administered to a nursing mother.

H. Pediatric Use

Estradiol/Norethindrone Acetate Tablets are not indicated in children

I. Geriatric Use

Clinical studies of Estradiol/Norethindrone Acetate Tablets did not include sufficient number of subjects aged 65 and over to determine if they responded differently from younger subjects.

Of the total number of subjects in the estrogen-plus-progestin substudy of the Women's Health Initiative (WHI) study, 44% (n=7,320) were 65-74 years of age, while 6.6% (n=1,095) were 75 years and over. There was a higher relative risk (CE/MPA vs. placebo) of non-fatal stroke and invasive breast cancer in women 75 and over compared to women less than 75 years of age. In women greater than 75, the increased risk of non-fatal stroke and invasive breast cancer observed in the estrogen-plus-progestin combination group compared to the placebo group was 75 vs. 24 per 10,000 women-years and 52 vs. 12 per 10,000 women-years, respectively.

In the estrogen-plus-progestin Women's Health Initiative Memory Study (WHIMS), a substudy of WHI, a population of 4,532 hysterectomized women, aged 65 to 79 years, was randomized to CE/MPA (0.625 mg/2.5 mg daily) or placebo. In the estrogen-plus-progestin group, after an average follow-up of four years, the relative risk (CE/MPA vs. placebo) of probable dementia was 2.05 (95% CI 1.21-3.48).The absolute risk of developing probable dementia with CE/MPA was 45 vs. 22 cases per 10,000 women-years with placebo.

Of the total number of subjects in the estrogen-alone substudy of WHI, 46% (n=4,943) were 65 years and over, while 7.1% (n=767) were 75 years and over. There was a higher relative risk (CE vs. placebo) of stroke in women less than 75 years of age compared to women 75 years and over. In the estrogen-alone WHIMS substudy, a population of 2,947 hysterectomized women, aged 65 to 79 years, was randomized to CE (0.625 mg daily) or placebo. After an average follow-up of 5.2 years, the relative risk (CE vs. placebo) of probable dementia was 1.49 (95% CI 0.83-2.66). The absolute risk of developing probable dementia with estrogen alone was 37 vs. 25 cases per 10,000 women-years with placebo.

Seventy-nine percent of the cases of probable dementia occurred in women that were older than 70 for the CE-alone group, and 82 percent of the cases of probable dementia occurred in women who were older than 70 in the CE/MPA group. The most common classification of probable dementia in both the treatment groups and placebo groups was Alzheimer's disease.

When data from the two populations were pooled as planned in the WHIMS protocol, the reported overall relative risk for probable dementia was 1.76 (95% CI 1.19-2.60). Since both substudies were conducted in women aged 65 to 79 years, it is unknown whether these findings apply to younger postmenopausal women. (See BOXED WARNINGS and WARNINGS, Dementia.)

ADVERSE REACTIONS

See BOXED WARNINGS, WARNINGS and PRECAUTIONS.

Because clinical trials are conducted under widely varying conditions, adverse reaction rates observed in the clinical trials of a drug cannot be directly compared to rates in the clinical trials of another drug and may not reflect the rates observed in practice. The adverse reaction information from clinical trials does, however, provide a basis for identifying the adverse events that appear to be related to drug use and for approximating rates.

Adverse events reported with Estradiol/Norethindrone Acetate Tablets 1.0 mg/0.5 mg by investigators in the Phase 3 studies regardless of causality assessment are shown in Table 6.

TABLE 6 ALL TREATMENT-EMERGENT ADVERSE EVENTS REGARDLESS OF RELATIONSHIP REPORTED AT A FREQUENCY OF ≥ 5% WITH ESTRADIOL/NORETHINDRONE ACETATE TABLETS 1.0 MG/0.5 MG
 | Endometrial Hyperplasia Study (12-Months) |  | Vasomotor Symptoms Study (3-Months) |  | Osteoporosis Study (2 years)
 | Estradiol/Norethindrone Acetate Tablets 1.0 mg/0.5 mg | 1 mg E2 | Estradiol/Norethindrone Acetate Tablets 1.0 mg/0.5 mg | Placebo | Estradiol/Norethindrone Acetate Tablets 1.0 mg/0.5 mg | Placebo
 | (n=295) | (n=296) | (n=29) | (n=34) | (n=47) | (n=48)
Body as a Whole
Back Pain | 6% | 5% | 3% | 3% | 6% | 4%
Headache | 16% | 16% | 17% | 18% | 11% | 6%
Digestive System
Nausea | 3% | 5% | 10% | 0% | 11% | 0%
Gastroenteritis | 2% | 2% | 0% | 0% | 6% | 4%
Nervous System
Insomnia | 6% | 4% | 3% | 3% | 0% | 8%
Emotional Lability | 1% | 1% | 0% | 0% | 6% | 0%
Respiratory System
Upper Respiratory Tract Infection | 18% | 15% | 10% | 6% | 15% | 19%
Sinusitis | 7% | 11% | 7% | 0% | 15% | 10%
Metabolic and Nutritional
Weight Increase | 0% | 0% | 0% | 0% | 9% | 6%
Urogenital System
Breast Pain | 24% | 10% | 21% | 0% | 17% | 8%
Post-Menopausal Bleeding | 5% | 15% | 10% | 3% | 11% | 0%
Uterine Fibroid | 5% | 4% | 0% | 0% | 4% | 8%
Ovarian Cyst | 3% | 2% | 7% | 0% | 0% | 8%
Resistance mechanism
Infection Viral | 4% | 6% | 0% | 3% | 6% | 6%
Moniliasis Genital | 4% | 7% | 0% | 0% | 6% | 0%
Secondary Terms
Injury Accidental | 4% | 3% | 3% | 0% | 17% [including one upper extremity fracture in each group] | 4%
Other Events | 2% | 3% | 3% | 0% | 6% | 4%

Adverse events reported with Estradiol/Norethindrone Acetate Tablets 0.5 mg/0.1 mg by investigators during the Phase 3 study regardless of causality assessment are shown in Table 7.

TABLE 7 ALL TREATMENT-EMERGENT ADVERSE EVENTS REGARDLESS OF RELATIONSHIP REPORTED AT A FREQUENCY OF ≥ 5% WITH ESTRADIOL/NORETHINDRONE ACETATE TABLETS 0.5 MG/0.1 MG
 | Estradiol/Norethindrone Acetate Tablets 0.5 mg/0.1 mg (n=194) | Placebo (n=200)
Body as a Whole
Back Pain | 10% | 4%
Headache | 22% | 19%
Pain in extremity | 5% | 4%
Digestive System
Nausea | 5% | 4%
Diarrhea | 6% | 6%
Respiratory System
Nasopharyngitis | 21% | 18%
Urogenital System
Endometrial thickening | 10% | 4%
Vaginal hemorrhage | 26% | 12%

The following adverse reactions have been reported with estrogen and/or progestin therapy:

1. Genitourinary system

Changes in vaginal bleeding pattern and abnormal withdrawal bleeding or flow; breakthrough bleeding; spotting; dysmenorrhea, increase in size of uterine leiomyomata; vaginitis, including vaginal candidiasis; change in amount of cervical secretion; changes in cervical ectropion; pre-menstrual-like syndrome; cystitis-like syndrome; ovarian cancer; endometrial hyperplasia; endometrial cancer.

2. Breasts

Tenderness, enlargement, pain, nipple discharge, galactorrhea; fibrocystic breast changes; breast cancer.

3. Cardiovascular

Deep and superficial venous thrombosis; pulmonary embolism; thrombophlebitis; myocardial infarction, stroke; increase in blood pressure.

4. Gastrointestinal

Nausea, vomiting; changes in appetite; cholestatic jaundice; abdominal pain/cramps, flatulence, bloating; increased incidence of gallbladder disease; pancreatitis; enlargement of hepatic hemangiomas.

5. Skin

Chloasma or melasma that may persist when drug is discontinued; erythema multiforme; erythema nodosum; hemorrhagic eruption; loss of scalp hair; seborrhea; hirsutism; itching; skin rash; pruritus.

6. Eyes

Retinal vascular thrombosis, intolerance to contact lenses.

7. Central nervous system

Headache; migraine; dizziness; mental depression; chorea; insomnia; nervousness; mood disturbances; irritability; exacerbation of epilepsy; probable dementia

8. Miscellaneous

Increase or decrease in weight; aggravation of porphyria; edema; leg cramps; changes in libido; fatigue; reduced carbohydrate tolerance; anaphylactoid/anaphylactic reactions; hypocalcemia; exacerbation of asthma; increased triglycerides; back pain; arthralgia; myalgia.

OVERDOSAGE

Serious ill effects have not been reported following acute ingestion of large doses of estrogen-containing drug products by young children. Overdosage of estrogen may cause nausea and vomiting, and withdrawal bleeding may occur in females.

DOSAGE AND ADMINISTRATION

Use of estrogen, alone or in combination with a progestin, should be with the lowest effective dose and for the shortest duration consistent with treatment goals and risks for the individual woman. Patients should be re-evaluated periodically as clinically appropriate (e.g., 3 to 6 month intervals) to determine if treatment is still necessary (See BOXED WARNINGS and WARNINGS). For women who have a uterus, adequate diagnostic measures, such as endometrial sampling, when indicated, should be undertaken to rule out malignancy in cases of undiagnosed persistent or recurring abnormal vaginal bleeding.

Estradiol/Norethindrone Acetate Tablets therapy consists of a single tablet to be taken once daily.

1. For the treatment of moderate to severe vasomotor symptoms associated with menopause, and the prevention of postmenopausal osteoporosis. When prescribing solely for the prevention of postmenopausal osteoporosis, therapy should only be considered for women at significant risk of osteoporosis and non-estrogen medications should be carefully considered.
  - Estradiol/Norethindrone Acetate Tablets 1.0 mg/0.5 mg
  - Estradiol/Norethindrone Acetate Tablets 0.5 mg/0.1 mg
2 For the treatment of moderate to severe symptoms of vulvar and vaginal atrophy. When used solely for the treatment of symptoms of vulvar and vaginal atrophy, topical vaginal products should be considered.
  - Estradiol/Norethindrone Acetate Tablets 1.0 mg/0.5 mg

Patients should be started at the lowest dose.

HOW SUPPLIED

Estradiol/Norethindrone Acetate Tablets 1.0 mg/0.5 mg are white, convex, coated tablets debossed with "B" on one side and "474" on the other side (NDC 54868-4677-0).

Estradiol/Norethindrone Acetate Tablets are supplied as: 28 tablets in a calendar blister pack dispenser.

STORAGE AND HANDLING

Store in a dry place protected from light. Store at 25°C (77°F), excursions permitted to 15-30°C (59-86°F). [See USP Controlled Room Temperature.]

WARNING: KEEP THIS AND ALL MEDICATIONS OUT OF REACH OF CHILDREN. IN THE CASE OF ACCIDENTAL OVERDOSE SEEK PROFESSIONAL ASSISTANCE OR CONTACT A POISON CONTROL CENTER IMMEDIATELY.

Rx Only

Distributed by:
Breckenridge Pharmaceutical, Inc.
Boca Raton, FL 33487

Manufactured by:
Pharmaceutics International, Inc.
Hunt Valley, Maryland 21031

ISSUED January 2010

Additional barcode labeling by:
Physicians Total Care, Inc.
Tulsa, Oklahoma 74146

PRINCIPAL DISPLAY PANEL - 1.0 mg / 0.5 mg Carton

NDC 54868-4677-0

Estradiol /
Norethindrone Acetate Tablets

1.0 mg / 0.5 mg

28 tablets
Rx only